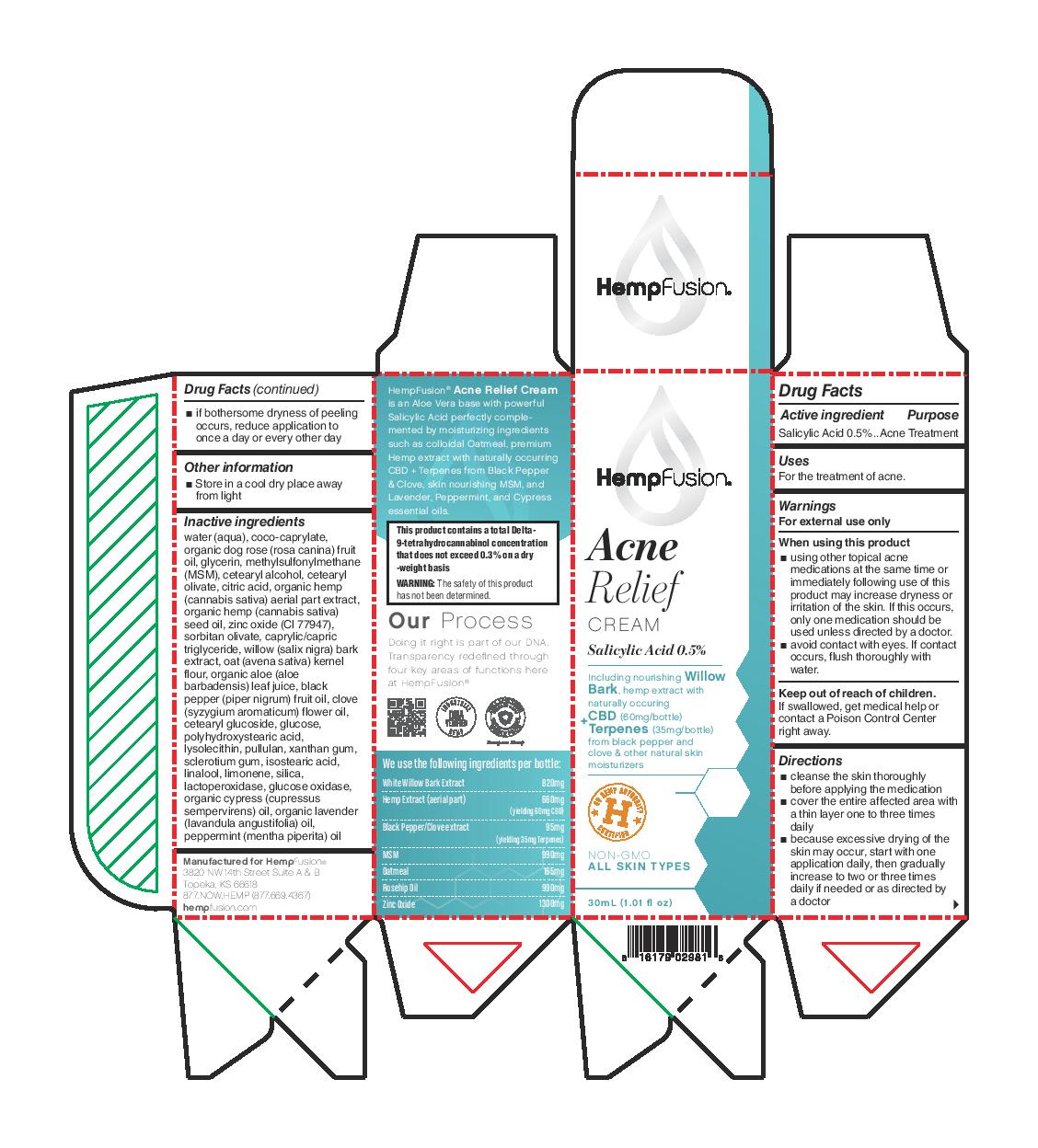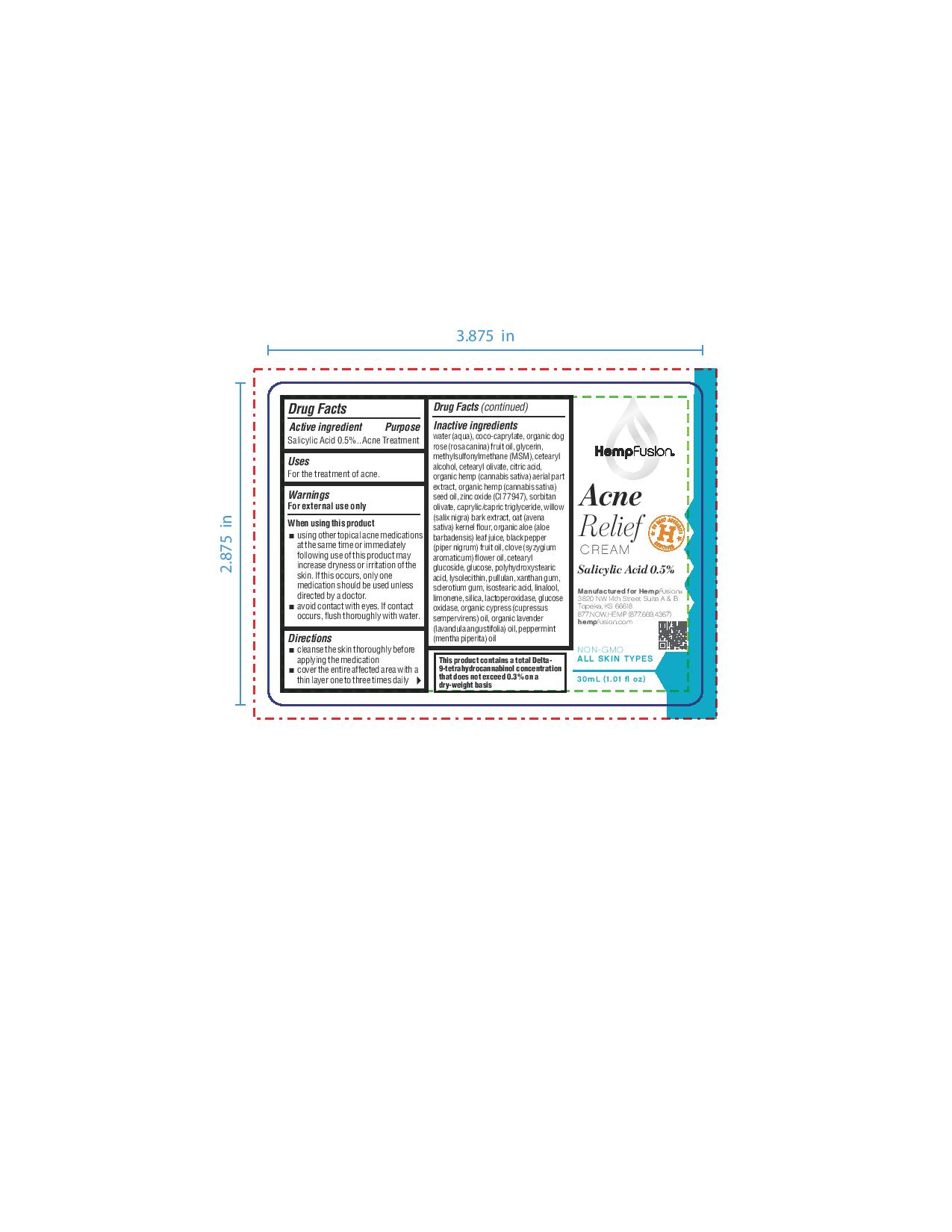 DRUG LABEL: Acne Relief Cream
NDC: 73672-981 | Form: CREAM
Manufacturer: HEMPFUSION, INC.
Category: otc | Type: HUMAN OTC DRUG LABEL
Date: 20210317

ACTIVE INGREDIENTS: SALICYLIC ACID 5 mg/1 mL
INACTIVE INGREDIENTS: BLACK PEPPER OIL; CLOVE OIL; CETEARYL GLUCOSIDE; PULLULAN; ISOSTEARIC ACID; LINALOOL, (+/-)-; LIMONENE, (+)-; SILICON DIOXIDE; GLUCOSE OXIDASE; LAVENDER OIL; GLYCERIN; CETEARYL OLIVATE; ROSA CANINA FRUIT OIL; CETOSTEARYL ALCOHOL; ANHYDROUS DEXTROSE; CUPRESSUS SEMPERVIRENS LEAF OIL; PEPPERMINT OIL; CANNABIS SATIVA SEED OIL; SORBITAN OLIVATE; OATMEAL; ALOE; LYSOPHOSPHATIDYLCHOLINE, SOYBEAN; MYELOPEROXIDASE; COCO-CAPRYLATE; DIMETHYL SULFONE; CITRIC ACID MONOHYDRATE; HEMP; ZINC OXIDE; MEDIUM-CHAIN TRIGLYCERIDES; WATER; POLYHYDROXYSTEARIC ACID (2300 MW); XANTHAN GUM; BETASIZOFIRAN; WILLOW BARK

Acne Relief Cream

Active ingredient

Salicylic Acid 0.5%

Purpose

Salicylic Acid 0.5%..Acne Treatment

Uses

For the treatment of acne.

Warnings

For external use only

When using this product

- using other topical acne medications at the same time or immediately following use of this product may increase dryness or irritation of the skin. If this occurs, only one medication should be used unless directed by a doctor.
- avoid contact with eyes. If contact occurs, flush thoroughly with water.

Keep out of reach of children. If swallowed, get medical help or contact a Poison Control Center right away.

Directions

- cleanse the skin thoroughly before applying the medication
- cover the entire affected area with a thin layer one to three times daily
- because excessive drying of the skin may occur, start with one application daily, then gradually increase to two or three times daily if needed or as directed by a doctor
- if bothersome dryness of peeling occurs, reduce application to once a day or every other day

Other information

- Store in a cool dry place away from light

Inactive ingredients

water (aqua), coco-caprylate, organic dog rose (rosa canina) fruit oil, glycerin, methylsulfonylmethane (MSM), cetearyl alcohol, cetearyl olivate, citric acid, organic hemp (cannabis sativa) aerial part extract, organic hemp (cannabis sativa) seed oil, zinc oxide (Cl 77947), sorbitan olivate, caprylic/capric triglyceride, willow (salix nigra) bark extract, oat (avena sativa) kernel flour, organic aloe (aloe barbadensis) leaf juice, black pepper (piper nigrum) fruit oil, clove (syzygium aromaticum) flower oil, cetearyl glucoside, glucose, polyhydroxystearic acid, lysolecithin, pullulan, xanthan gum, sclerotium gum, isostearic acid, linalool, limonene, silica, lactoperoxidase, glucose oxidase, organic cypress (cupressus sempervirens) oil, organic lavender (lavandula angustifolia) oil, peppermint (mentha piperita) oil

QUESTIONS

Manufactured for HempFusion(r)

3820 NW 14th Street Suite A & B

Topeka, ks 66618

877.NOW.HEMP (877.669.4367)

hempfusion.com

PACKAGE LABEL

HempFusion

Acne

Relief

CREAM

Salicylic Acid 0.5%

Including nourishing Willow Bark, hemp extract with naturally occuring CBD (60mg/bottle) + Terpenes (35mg/bottle) from black pepper and clove & other natural skin moisturizers

US HEMP AUTHORITY H CERTIFIED

NON-GMO

ALL SKIN TYPES

30mL (1.01 fl oz)